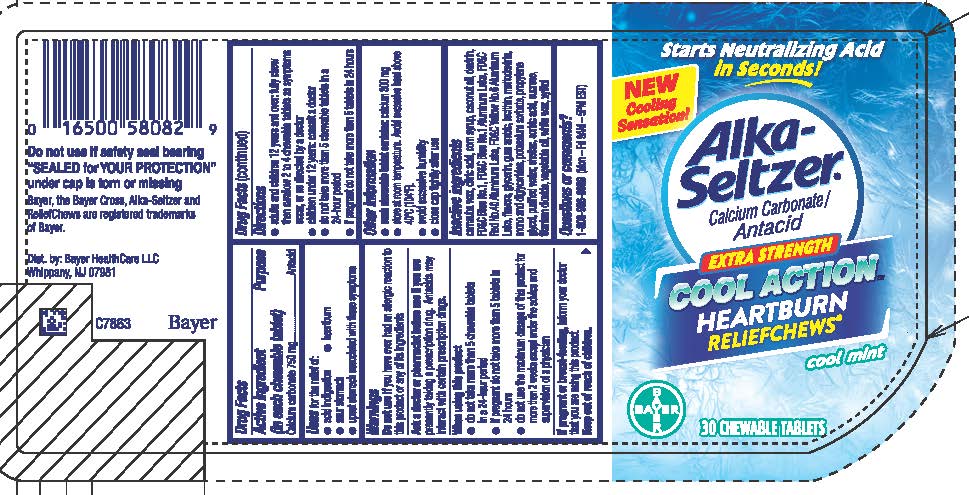 DRUG LABEL: Alka-Seltzer Cool Action Extra Strength ReliefChews Mint
NDC: 0280-0058 | Form: TABLET, CHEWABLE
Manufacturer: Bayer HealthCare LLC.
Category: otc | Type: HUMAN OTC DRUG LABEL
Date: 20251204

ACTIVE INGREDIENTS: CALCIUM CARBONATE 750 mg/1 1
INACTIVE INGREDIENTS: GLYCERIN; WATER; CORN SYRUP; PROPYLENE GLYCOL; SHELLAC; WHITE WAX; FD&C BLUE NO. 1; FD&C BLUE NO. 1--ALUMINUM LAKE; MALTODEXTRIN; TITANIUM DIOXIDE; SUCROSE; SORBIC ACID; XYLITOL; POTASSIUM SORBATE; CARNAUBA WAX; COCONUT OIL

Alka-Seltzer Cool Action Extra Strength Heartburn ReliefChews - Mint UI 1614266

Active ingredient (in each chewable tablet)

Calcium carbonate 750 mg

Purpose

Antacid

Uses

Uses for the relief of:

● acid indigestion ● heartburn ● sour stomach

● upset stomach associated with these symptoms

Warnings

Do not use if you have ever had an allergic reaction to this product or any of its ingredients

Ask a doctor or pharmacist before use if you are presently taking a prescription drug. Antacids may interact with certain prescription drugs.

When using this product
● do not take more than 5 chewable tablets in a 24-hour
period

● if pregnant do not take more than 5 tablets in 24 hours

● do not use the maximum dosage of this product for more

than 2 weeks except under the advice and supervision of a

physician

PREGNANCY OR BREAST FEEDING

If pregnant or breast-feeding, inform your doctor that you are using this product.

Keep out of reach of children.

Directions

● adults and children 12 years and over: fully chew then swallow 2 to 4 chewable tablets as symptoms occur, or as directed by a doctor

● children under 12 years: consult a doctor

● do not take more than 5 chewable tablets in a 24-hour period

● if pregnant, do not take more than 5 chewable tablets in 24

hours

Other information

● each chewable tablet contains: calcium 300 mg

● store at room temperature. Avoid excessive heat above 40ºC (104ºF).

● avoid excessive humidity

● close cap tightly after use

INACTIVE INGREDIENT

Inactive ingredients carnauba wax, citric acid, coconut oil, corn syrup, dextrin, FD&C Blue No.1, FD&C Blue No.1 Aluminum Lake, FD&C Red No.40 Aluminum Lake, FD&C Yellow No.6 Aluminum Lake, flavors, glycerin, gum arabic, lecithin, maltodextrin, mono and diglycerides, potassium sorbate, propylene glycol, purified water, shellac, sorbic acid, sucrose, titanium dioxide, vegetable oil, white wax, xylitol

Questions or comments? 1-800-986-0369

(Mon – Fri 9AM – 5PM EST)

Bottle label 30 tablets

Starts Neutralizing Acid

in Seconds!

NEW

Cooling

Sensation

Alka-Seltzer®

Calcium Carbonate/Antacid

EXTRA STRENGTH

COOL ACTION

HEARTBURN

RELIEFCHEWS®

cool mint

30 Chewable Tablets